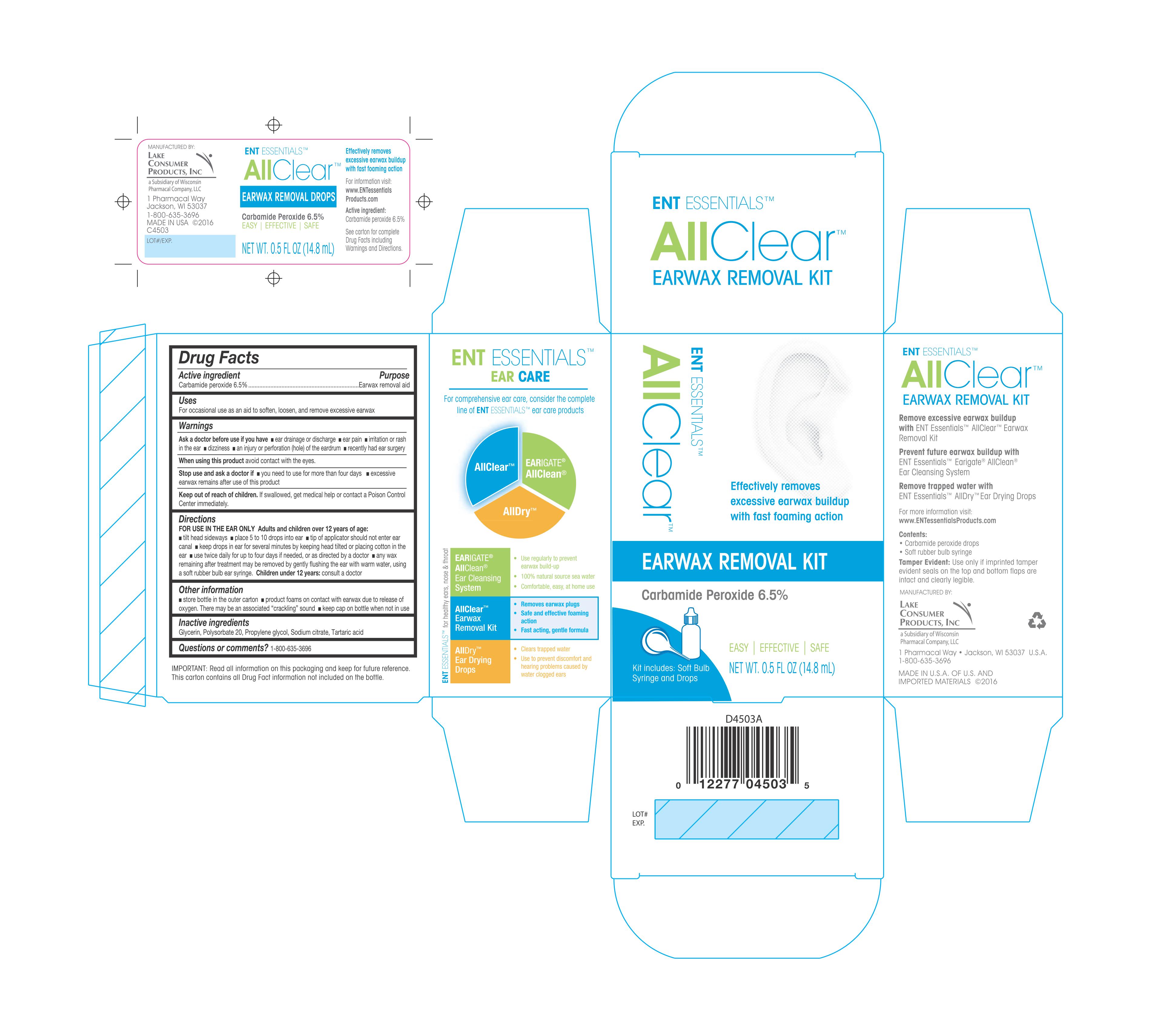 DRUG LABEL: ENT Essentials Ear Wax Remvoer
NDC: 68093-4503 | Form: LIQUID
Manufacturer: Wisconsin Pharmacal Company
Category: otc | Type: HUMAN OTC DRUG LABEL
Date: 20171108

ACTIVE INGREDIENTS: CARBAMIDE PEROXIDE 0.065 g/1 g
INACTIVE INGREDIENTS: TARTARIC ACID; GLYCERIN; PROPYLENE GLYCOL; SODIUM CITRATE; POLYSORBATE 20

Active Ingredient

Carbamide Peroxide 6.5%

Purpose

Earwax removal aid

Uses

For occasional use as an aid to soften, loosen, and remove excessive earwax.

Warnings

Aska doctor before use if you have

- ear drainage or discharge
- ear pain
- irritation or rash in the ear
- dizziness
- an injury or perforation (hole) of the eardrum
- recently had ear surgery

When using this product avoid contact wtih the eyes

Stop use and aks a doctor if

- you need to use for more than four days
- excessive earwax remains after use of this product

Keep out of reach of children. If swallowed, get medical help or contact a Poison Control Center immediately.

DOSAGE AND ADMINISTRATION

D irections

FOR USE IN THE EAR ONLY Adults and children over 12 years of age:

tilt head sideways
place 5 to 10 drops into ear
tip of applicator should not enter ear canal
keep drops in ear for several minutes by keeping head tilted or placing cotton in the ear
use twice daily for up to four days if needed, or as directed by a doctor
any wax remaining after treatment may be removed by gently flusing the ear with warm water, using a soft rubber bulb ear syringe.

Children under 12 years: consult a doctor.

Other informaiton

- store bottle in teh outer carton
- product foams on contact with earwax due to the release of oxygen. Theremay be an associated "crackling" sound
- keep cap on bottle when not in use

Inactive ingredients

Glycerin, Polysorbate 20, Propylene glycol, Sodium citrate, Tartaric acid

Questions or comments? 1-800-635-3696